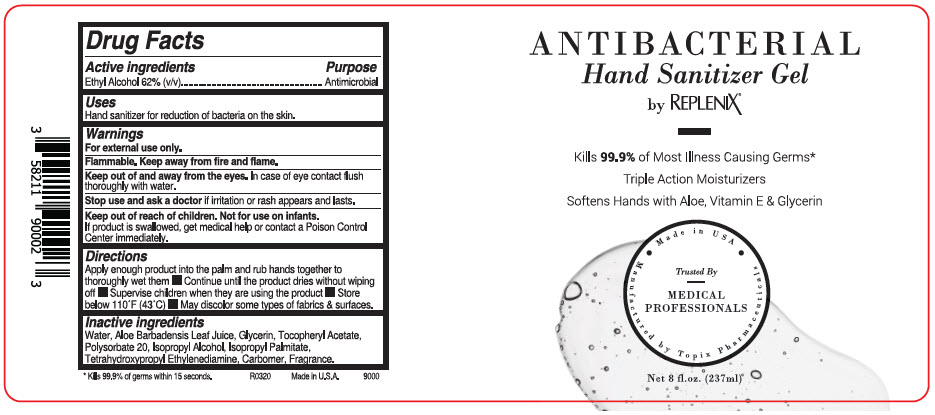 DRUG LABEL: Sanix Alcohol Hand Rub
NDC: 51326-900 | Form: LIQUID
Manufacturer: Topiderm, Inc
Category: otc | Type: HUMAN OTC DRUG LABEL
Date: 20200324

ACTIVE INGREDIENTS: ALCOHOL 0.62 mL/1 mL
INACTIVE INGREDIENTS: ISOPROPYL PALMITATE; CARBOMER HOMOPOLYMER TYPE C (ALLYL PENTAERYTHRITOL CROSSLINKED); WATER; EDETOL; ISOPROPYL ALCOHOL; .ALPHA.-TOCOPHEROL ACETATE; POLYSORBATE 20; GLYCERIN

Sanix Alcohol Hand Rub

Drug Facts

Active ingredients

Ethyl Alcohol 62% (v/v)

Purpose

Antimicrobial

Uses

Hand sanitizer for reduction of bacteria on the skin.

Warnings

For external use only.

Flammable. Keep away from fire and flame.

Keep out of and away from the eyes. In case of eye contact flush thoroughly with water.

Stop use and ask a doctor if irritation or rash appears and lasts.

Keep out of reach of children. Not for use on infants.

If product is swallowed, get medical help or contact a Poison Control Center immediately.

Directions

Apply enough product into the palm and rub hands together to thoroughly wet them

- Continue until the product dries without wiping off
- Supervise children when they are using the product
- Store below 110°F (43°C)
- May discolor some types of fabrics & surfaces.

Inactive ingredients

Water, Aloe Barbadensis Leaf Juice, Glycerin, Tocopheryl Acetate, Polysorbate 20, Isopropyl Alcohol, Isopropyl Palmitate, Tetrahydroxypropyl Ethylenediamine, Carbomer, Fragrance.

PRINCIPAL DISPLAY PANEL - 237 ml Bottle Label

ANTIBACTERIAL
Hand Sanitizer Gel
by REPLENIX®

Kills 99.9% of Most Illness Causing Germs*
Triple Action Moisturizers
Softens Hands with Aloe, Vitamin E & Glycerin

Made in USA
Trusted By
MEDICAL
PROFESSIONALS
Manufactured by Topix Pharmaceuticals

Net 8 fl.oz. (237ml)